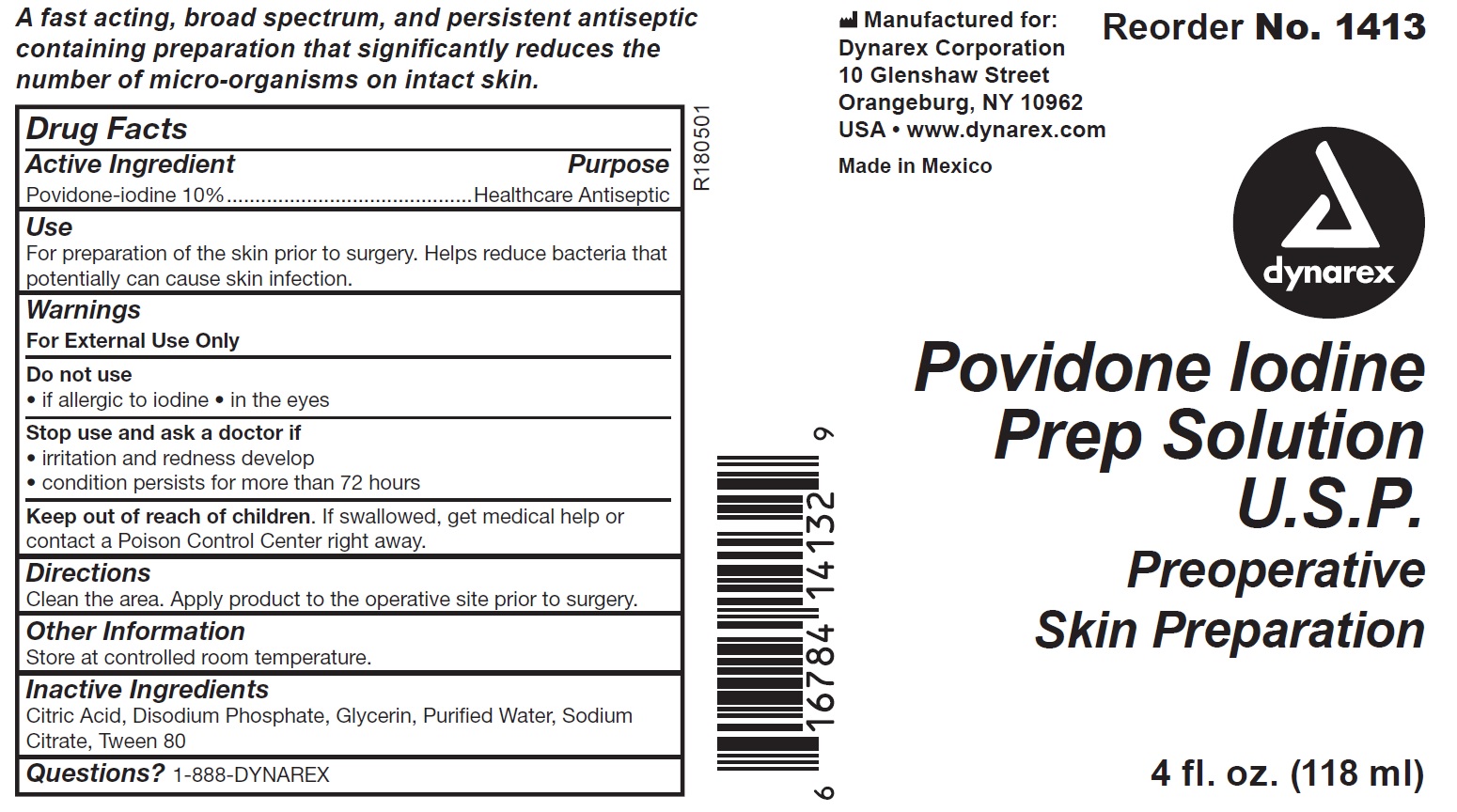 DRUG LABEL: Dynarex Povidone Iodine Prep Solution
NDC: 67777-141 | Form: LIQUID
Manufacturer: Dynarex Corporation
Category: otc | Type: HUMAN OTC DRUG LABEL
Date: 20241120

ACTIVE INGREDIENTS: POVIDONE-IODINE 10 mg/1 mL
INACTIVE INGREDIENTS: GLYCERIN; CITRIC ACID MONOHYDRATE; WATER; POLYSORBATE 80; SODIUM PHOSPHATE; SODIUM CITRATE

1413, 1414, 1415, 1416

Active Ingredient

Povidone-iodine 10%

Purpose

Healthcare Antiseptic

Use

For preparation of the skin prior to surgery. Helps reduce bacteria that potentially can cause skin infection

Warnings

For external use only

Do Not Use

- if allergic to iodine
- in the eyes

Stop use and ask a doctor if

- irritation and redness develop
- condition persists for more than 72 hours

Keep out of reach of children. If swallowed, get medical help or contact a Poison Control Center right away.

Directions

Clean the area. Apply product to the operative site prior to surgery.

Other

Store at controlled room temperature.

Inactive Ingredients

Citric Acid, Disodium Phosphate, Glycerin, Puried Water, Sodium Citrate, Tween 80

Questions?

1-888-DYNAREX